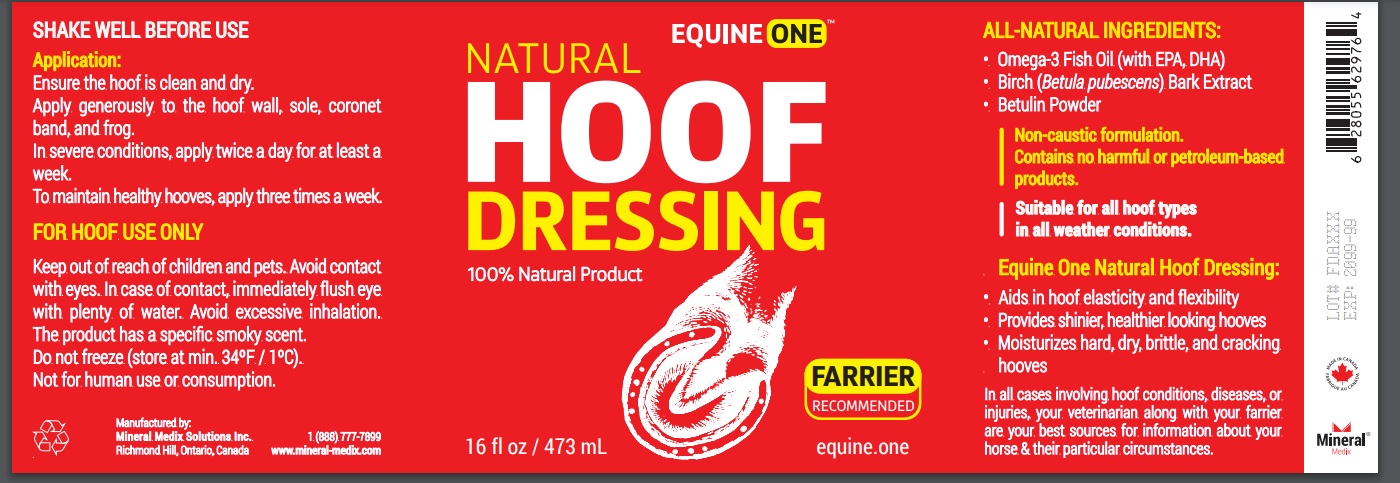 DRUG LABEL: Equine One Hoof Dressing
NDC: 86142-001 | Form: OINTMENT
Manufacturer: Mineral Medix Solutions Inc.
Category: animal | Type: OTC ANIMAL DRUG LABEL
Date: 20210702

ACTIVE INGREDIENTS: OMEGA-3 FATTY ACIDS 79 g/100 mL; BETULA PUBESCENS BARK 20 g/100 mL; BETULIN 1 g/100 mL

Active Ingredient

Omega-3 Fatty Acid, Betula Pubescens Bark, Betulin

Purpose

Topical hoof oil to help with most common hoof related issues

Use

• Aids in hoof elasticity and flexibility
• Provides shinier, healthier looking hooves
• Moisturizes hard, dry, brittle, and cracking hooves

Non-caustic formulation.
Contains no harmful or petroleum-based products.
Suitable for all hoof types in all weather conditions.

Warnings

FOR HOOF USE ONLY

Keep out of reach of children and pets.
Avoid contact with eyes.
In case of contact, immediately flush eye with plenty of water.
Avoid excessive inhalation.
The product has a specific smoky scent.
Do not freeze (store at min. 34ºF / 1ºC).
Not for human use or consumption.

In all cases involving hoof conditions, diseases, or injuries, your veterinarian along with your farrier are your best sources for information about your horse & their particular circumstances.

Application

SHAKE WELL BEFORE USE

Ensure the hoof is clean and dry.
Apply generously to the hoof wall, sole, coronet band, and frog.
In severe conditions, apply twice a day for at least a week.
To maintain healthy hooves, apply three times a week.